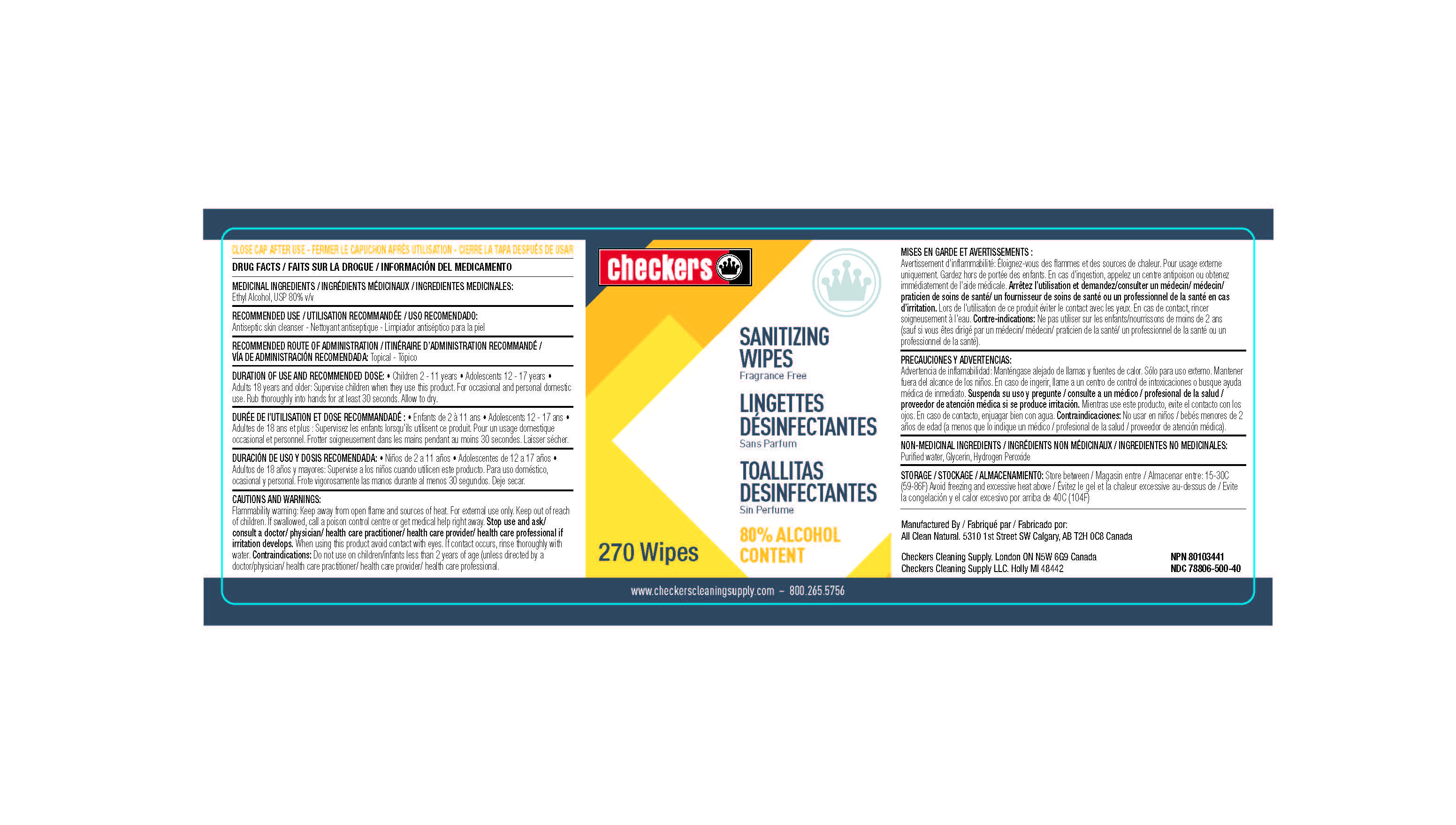 DRUG LABEL: Hand Sanitizer
NDC: 78806-500 | Form: CLOTH
Manufacturer: All Clean Natural Ltd.
Category: otc | Type: HUMAN OTC DRUG LABEL
Date: 20201009

ACTIVE INGREDIENTS: ALCOHOL 80 mL/100 mL
INACTIVE INGREDIENTS: GLYCERIN 1.45 mL/100 mL; HYDROGEN PEROXIDE 0.125 mL/100 mL; WATER

Checkers Sanitizing Wipes

This is a hand sanitizer manufactured according to the Temporary Policy for Preparation of Certain Alcohol-Based Hand Sanitizer Products During the Public Health Emergency (CoViD-19); Guidance for Industry.

The hand sanitizer is manufactured using only the following United States Pharmacopoeia (USP) grade ingredients in the preparation of the product (percentage in final product formulation) consistent with World Health Organization (WHO) recommendations:

1. Alcohol (ethanol) (USP or Food Chemical Codex (FCC) grade) (80%, volume/volume (v/v)) in an aqueous solution denatured according to Alcohol and Tobacco Tax and Trade Bureau regulations in 27 CFR part 20.
2. Glycerol (1.45% v/v).
3. Hydrogen peroxide (0.125% v/v).
4. Sterile distilled water or boiled cold water.

The firm does not add other active or inactive ingredients. Different or additional ingredients may impact the quality and potency of the product.

MEDICINAL INGREDIENTS

Ethyl Alcohol, USP 80% v/v

RECOMMENDED USE

Antiseptic skin cleanser

DURATION OF USE AND RECOMMENDED DOSE:

• Children 2 - 11 years • Adolescents 12 - 17 years • Adults 18 years and older: Supervise children when they use this product. For occasional and personal domestic use. Rub thoroughly into hands for at least 30 seconds. Allow to dry.

CAUTIONS AND WARNINGS:

Flammability warning: Keep away from open flame and sources of heat. For external use only. Keep out of reach of children. If swallowed, call a poison control centre or get medical help right away.

Contraindications:

Do not use on children/infants less than 2 years of age (unless directed by a doctor/physician/ health care practitioner/ health care provider/ health care professional.

When using this product avoid contact with eyes. If contact occurs, rinse thoroughly with water.

Stop use and ask/ consult a doctor/ physician/ health care practitioner/ health care provider/ health care professional if irritation develops.

Keep out of reach of children. If swallowed, get medical help or contact a Poison Control Center right away.

Directions

Children 2 - 11 years • Adolescents 12 - 17 years • Adults 18 years and older: Supervise children when they use this product. For occasional and personal domestic use. Rub thoroughly into hands for at least 30 seconds. Allow to dry.

Other information

- Store between 15-30C (59-86F)
- Avoid freezing and excessive heat above 40C (104F)

Inactive ingredients

glycerin, hydrogen peroxide, purified water